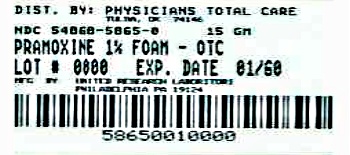 DRUG LABEL: Pramoxine Hydrochloride
NDC: 54868-5865 | Form: AEROSOL, FOAM
Manufacturer: Physicians Total Care, Inc.
Category: otc | Type: HUMAN OTC DRUG LABEL
Date: 20120523

ACTIVE INGREDIENTS: pramoxine hydrochloride 150 mg/15 g
INACTIVE INGREDIENTS: cetyl alcohol; glyceryl monostearate; methylparaben; polyoxyl 40 stearate; propylene glycol; propylparaben; water; trolamine; isobutane; propane

proctofoam®
non-steroid
(pramoxine hydrochloride 1%)

Drug Facts

Active ingredient

Pramoxine hydrochloride 1%

Purpose

Local Anesthetic

Use

for the temporary relief of pain and itching associated with hemorrhoids

Warnings

ASK DOCTOR

Do not exceed the recommended daily dosage unless directed by a physician.

If condition worsens or does not improve within 7 days, consult a physician.

In case of rectal bleeding, consult a physician promptly.

WHEN USING

Do not put this product into the rectum by using fingers or any mechanical device or applicator. Do not insert any part of the aerosol container into the rectum.

STOP USE

Certain persons can develop allergic reactions to the ingredients in this product. If the symptom being treated does not subside or if redness, irritation, swelling, pain or other symptoms develop or increase, discontinue use and consult a physician.

Keep out of reach of children. If swallowed, get medical help or contact a Poison Control Center right away.

Directions

- Place cap on container. Shake well before use.
- Adults: When practical, cleanse the affected area with mild soap and warm water and rinse thoroughly.
- Gently dry by patting or blotting with toilet tissue or a soft cloth before application of proctofoam®.
- Dispense proctofoam® onto a clean tissue and apply externally to the affected area up to 5 times daily.
- Children under 12 years of age: consult a physician.

Other information

- Store upright at controlled room temperature 20° - 25°C (68° - 77°F); excursions permitted between 15° - 30°C (59° - 86°F).
- Do not refrigerate.
- Contents of the container are under pressure. Do not burn or puncture the aerosol container.
- Do not store at temperatures above 120°F (49°C).

Inactive ingredients

cetyl alcohol, glyceryl monostearate and PEG-100 stearate blend, methylparaben, polyoxyethylene 23 lauryl ether, polyoxyl 40 stearate, propylene glycol, propylparaben, purified water, trolamine and inert propellants: isobutane and propane.

Questions?

1-888-317-0001

ALAVEN®
PHARMACEUTICAL LLC
Marietta, GA 30067, USA

Rev. 08/08

Additional barcode labeling by:
Physicians Total Care, Inc.
Tulsa, Oklahoma 74146

PRINCIPAL DISPLAY PANEL - 15 g Carton

NDC 54868-5865-0

STORE UPRIGHT

proctofoam®
non-
steroid
(pramoxine hydrochloride 1%)

hemorrhoidal foam

For temporary
relief of
hemorrhoidal
pain and itching

For External Use Only

15 g net wt (0.53 oz)